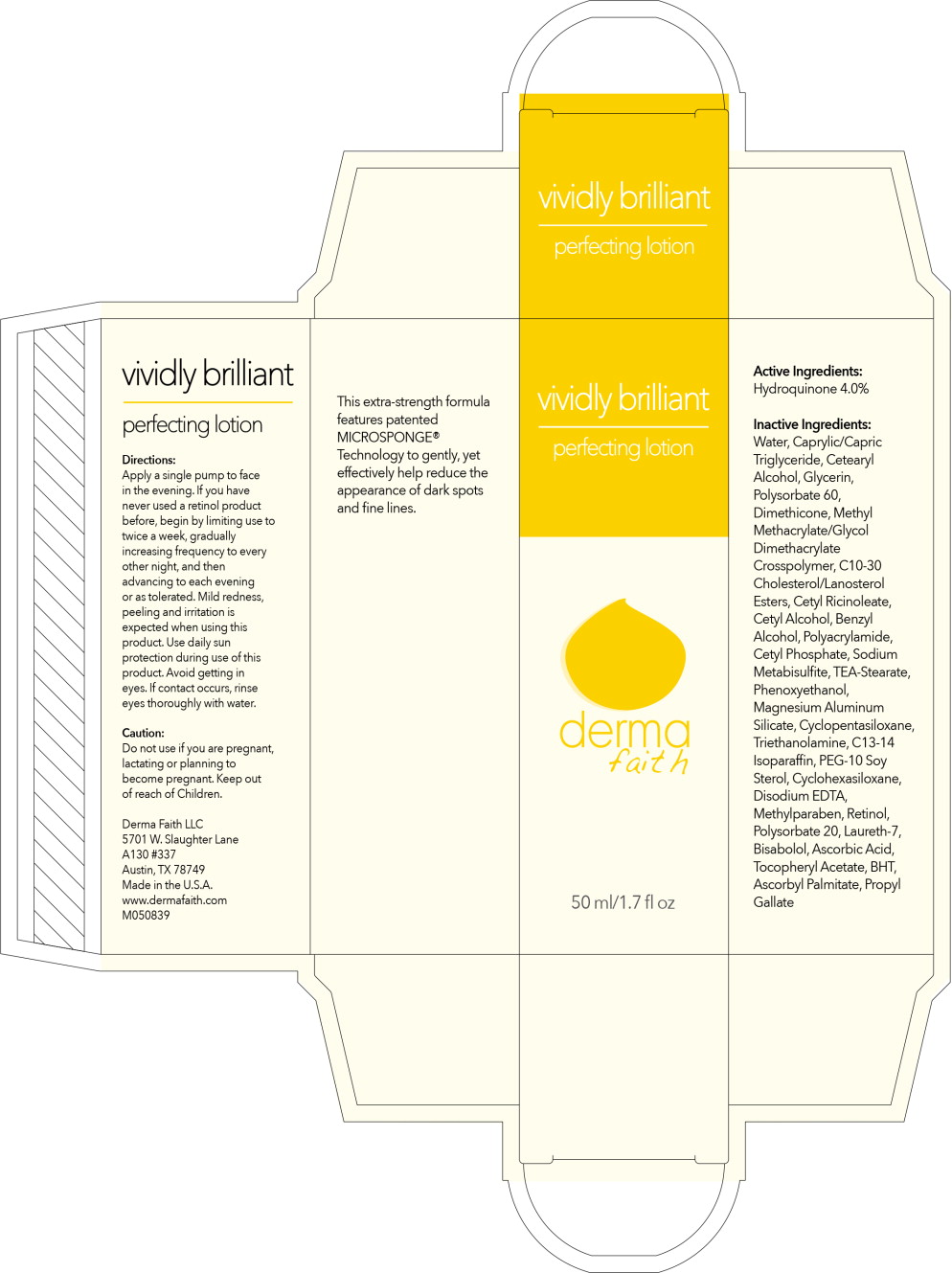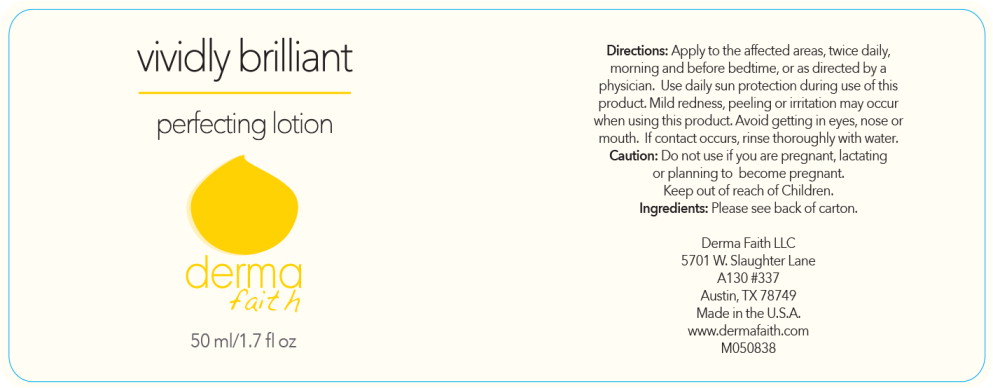 DRUG LABEL: Vividly Brilliant Perfecting
NDC: 68634-051 | Form: LIQUID
Manufacturer: AMCOL Health & Beauty Solutions, Inc. DBA
Category: otc | Type: HUMAN OTC DRUG LABEL
Date: 20150603

ACTIVE INGREDIENTS: hydroquinone 40 g/2 mL
INACTIVE INGREDIENTS: water; medium-chain triglycerides; cetostearyl alcohol; glycerin; polysorbate 60; dimethicone; methyl methacrylate/glycol dimethacrylate crosspolymer; C10-30 cholesterol/lanosterol esters; cetyl ricinoleate; cetyl alcohol; benzyl alcohol; cetyl phosphate; sodium metabisulfite; trolamine Stearate; phenoxyethanol; magnesium aluminum silicate; cyclomethicone 5; trolamine; C13-14 isoparaffin; PEG-10 soy sterol; cyclomethicone 6; edetate disodium; methylparaben; retinol; polysorbate 20; Laureth-7; levomenol; ascorbic acid; .alpha.-tocopherol acetate, DL-; butylated hydroxytoluene; ascorbyl palmitate; propyl gallate

Vividly Brilliant Perfecting Lotion

HBS Code (Labeler): FP60402-50.2
Distributor: Derma Faith

Human Prescription Drug
Active Ingredient: Hydroquinone 4%

CARTON TEXT

________________________________________________________

vividly brilliant
perfecting lotion

derma faith

50 ml/1.7 fl oz

vividly brilliant
perfecting lotion

Directions:

Apply a single pump to face in the evening. If you have never used a retinol product before, begin by limiting use to twice a week, gradually increasing frequency to every other night, and then advancing to each evening or as tolerated. Mild redness, peeling and irritation is expected when using this product.

INDICATIONS AND USAGE

Use daily sun protection during use of this product. Avoid getting in eyes. If contact occurs, rinse eyes thoroughly with water.

Caution:

Do not use if you are pregnant, lactating or planning to become pregnant.

Keep out of reach of children.

Derma Faith LLC
5701 W. Slaughter Lane
A130 #337
Austin, TX 78749
Made in the U.S.A.
www.dermafaith.com
M050839

This extra-strength formula features patented MICROSPONGE® Technology to gently, yet effectively help reduce the appearance of dark spots and fine lines.

Active Ingredients:

Hydroquinone 4.0%

Inactive Ingredients:

Water, Caprylic/Capric, Triglyceride, Cetearyl Alcohol, Glycerin, Polysorbate 60, Dimethicone, Methyl Methacrylate/Glycol Dimethacrylate Crosspolymer, C10-30 Cholesterol/Lanosterol Esters, Cetyl Ricinoleate, Cetyl Alcohol, Benzyl Alcohol, Polyacrylamide, Cetyl Phosphate, Sodium Metabisulfite, TEA-Stearate, Phenoxyethanol, Magnesium Aluminum Silicate, Cyclopentasiloxane, Triethanolamine, C13-14 Isoparaffin, PEG-10 Soy Sterol, Cyclohexasiloxane, Disodium EDTA, Methylparaben, Retinol, Polysorbate 20, Laureth-7, Bisabolol, Ascorbic Acid, Tocopheryl Acetate, BHT, Ascorbyl Palmitate, Propyl Gallate

________________________________________________________

150609

AMCOL Health & Beauty Solutions, Inc. DBA
301 Laser Lane Lafayette, LA 70507 | www.amcolhpc.com
lauren.haase@amcol.com

Principal Display Panel - Carton Label

vividly brilliant

perfecting lotion

derma
faith

50 ml/1.7 fl oz

Principal Display Panel - Bottle Label

vividly brilliant

perfecting lotion

derma
faith

50 ml/1.7 fl oz